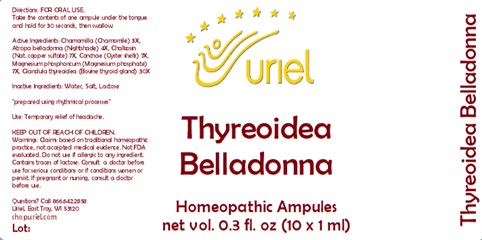 DRUG LABEL: Thyreoidea Belladonna
NDC: 48951-9357 | Form: LIQUID
Manufacturer: Uriel Pharmacy Inc.
Category: homeopathic | Type: HUMAN OTC DRUG LABEL
Date: 20240215

ACTIVE INGREDIENTS: CHAMOMILE 3 [hp_X]/1 mL; CUPRIC SULFATE 7 [hp_X]/1 mL; OSTREA EDULIS SHELL 7 [hp_X]/1 mL; THYROID, UNSPECIFIED 30 [hp_X]/1 mL; ATROPA BELLADONNA 4 [hp_X]/1 mL; MAGNESIUM PHOSPHATE, TRIBASIC, PENTAHYDRATE 7 [hp_X]/1 mL
INACTIVE INGREDIENTS: WATER; SODIUM CHLORIDE; LACTOSE

Thyreoidea Belladonna

INDICATIONS AND USAGE

Directions: FOR ORAL USE.

DOSAGE AND ADMINISTRATION

Take the contents of one ampule under the tongue and hold for 30 seconds, then swallow.

ACTIVE INGREDIENT

Active Ingredients: Chamomilla (Chamomile) 3X, Atropa belladonna (Nightshade) 4X, Chalkosin (Nat. copper sulfate) 7X, Conchae (Oyster shells) 7X, Magnesium phosphoricum (Magnesium phosphate) 7X, Glandula thyreoidea (Bovine thyroid gland) 30X

Inactive Ingredients: Water, Salt, Lactose

"prepared using rhythmical processes"

PURPOSE

Use: Temporary relief of headache.

KEEP OUT OF REACH OF CHILDREN.

WARNINGS

Warnings: Claims based on traditional homeopathic practice, not accepted medical evidence. Not FDA evaluated. Do not use if allergic to any ingredient. Contains traces of lactose. Consult a doctor before use for serious conditions or if conditions worsen or persist. If pregnant or nursing, consult a doctor before use.

QUESTIONS

Questions? Call 866.642.2858 Uriel, East Troy, WI 53120 shopuriel.com Lot: